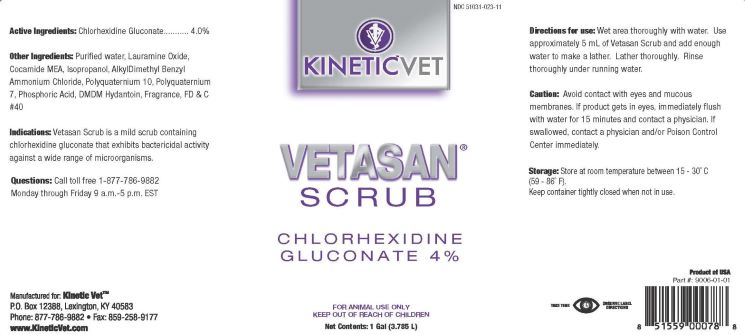 DRUG LABEL: VETASAN SCRUB
NDC: 51031-023 | Form: SOLUTION
Manufacturer: Kinetic Technologies LLC
Category: animal | Type: OTC ANIMAL DRUG LABEL
Date: 20231127

ACTIVE INGREDIENTS: CHLORHEXIDINE GLUCONATE 4 g/0.100 L
INACTIVE INGREDIENTS: LAURAMINE OXIDE; COCAMIDE; ISOPROPYL ALCOHOL; BENZALKONIUM CHLORIDE; POLYQUATERNIUM-7 (70/30 ACRYLAMIDE/DADMAC; 1600 KD); POLYQUATERNIUM-10 (1000 MPA.S AT 2%); PHOSPHORIC ACID; DMDM HYDANTOIN; FD&C RED NO. 40; WATER

VETASAN® SCRUB

Active Ingredients:

Chlorhexidine Gluconate........4.0%

Other Ingredients:

Purified water, Lauramine Oxide, Cocamide MEA, Isopropanol, AlkylDimethyl Benzyl Ammonium Chloride, Polyquaternium 10, Polyquaternium 7, Phosphoric Acid, DMDM Hydantoin, Fragrance, FD&C #40

Indications:

Vetasan Scrub is a mild scrub containing chlorhexidine gluconate that exhibits bactericidal activity against a wide range of microorganisms.

Questions:

Call toll free 1-877-786-9882

Monday through Friday 9 a.m. - 5 p.m. EST

Manufactured for: Kinetic Vet™

P.O. Box 12388, Lexington, KY 40583

Phone: 877-786-9882 • Fax: 859-258-9177

www.KineticVet.com

Directions for use:

Wet area thoroughly with water. Use approximately 5 mL of Vetasan Scrub and add enough water to make a lather. Lather thoroughly. Rinse thoroughly under running water.

Caution:

Avoid contact with eyes and mucous membranes. If product gets in eyes, immediately flush with water for 15 minutes and contact a physician. If swallowed, contact a physician and/or Poison Control Center immediately.

Storage:

Store at room temperature between 15 - 30°C (59 - 86°F).

Keep container tightly closed when not in use.

Product of USA

Part #9006-01-01

TAKE TIME OBSERVE LABEL INSTRUCTIONS

Net Contents: 1 Gal (3.785 L)

WARNINGS

FOR ANIMAL USE ONLY

KEEP OUT OF REACH OF CHILDREN

KINETIC™VET

VETASAN® SCRUB

CHLORHEXIDINE GLUCONATE 4%

FOR ANIMAL USE ONLY

KEEP OUT OF REACH OF CHILDREN

Net Contents: 1 Gal (3.785 L)